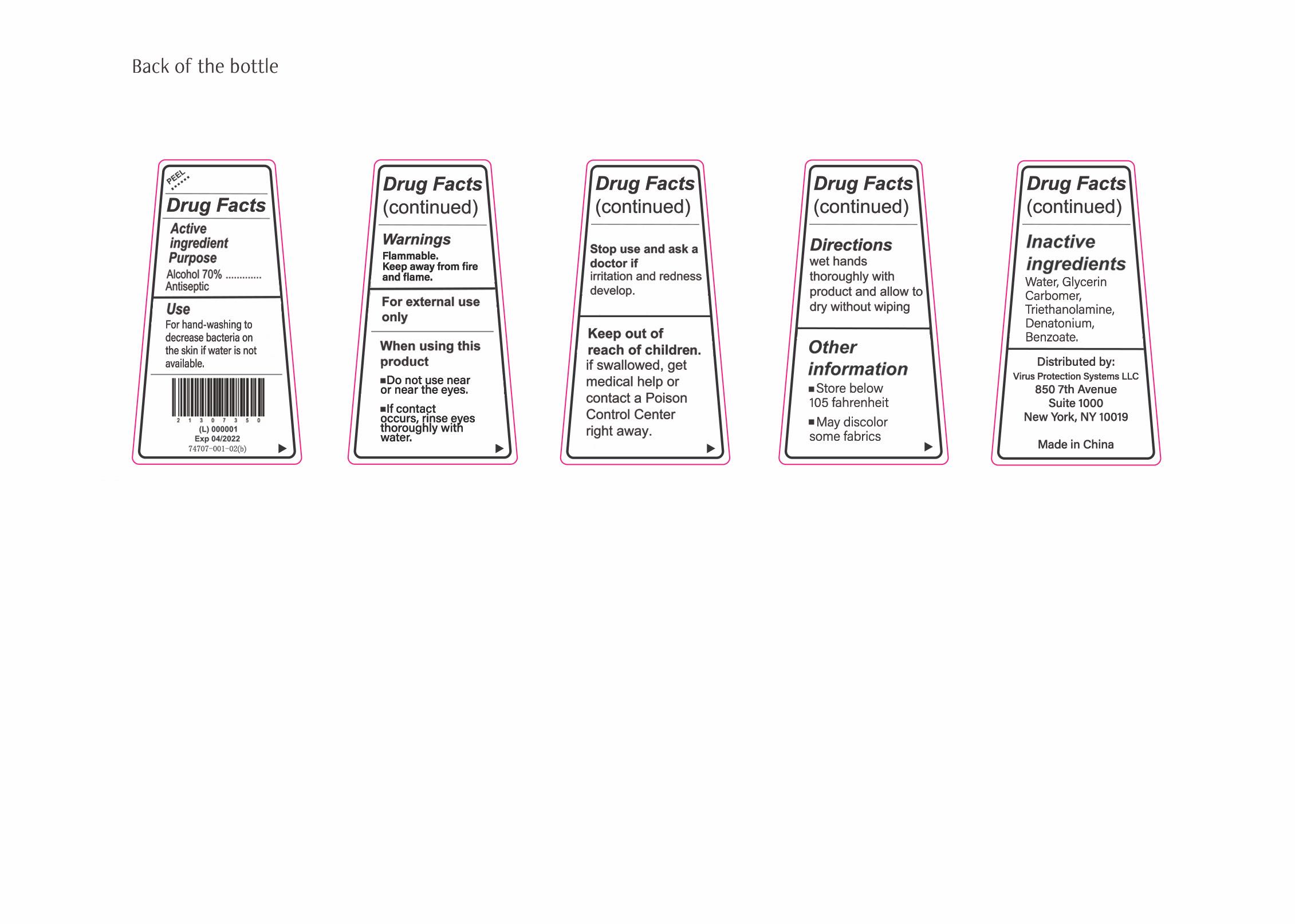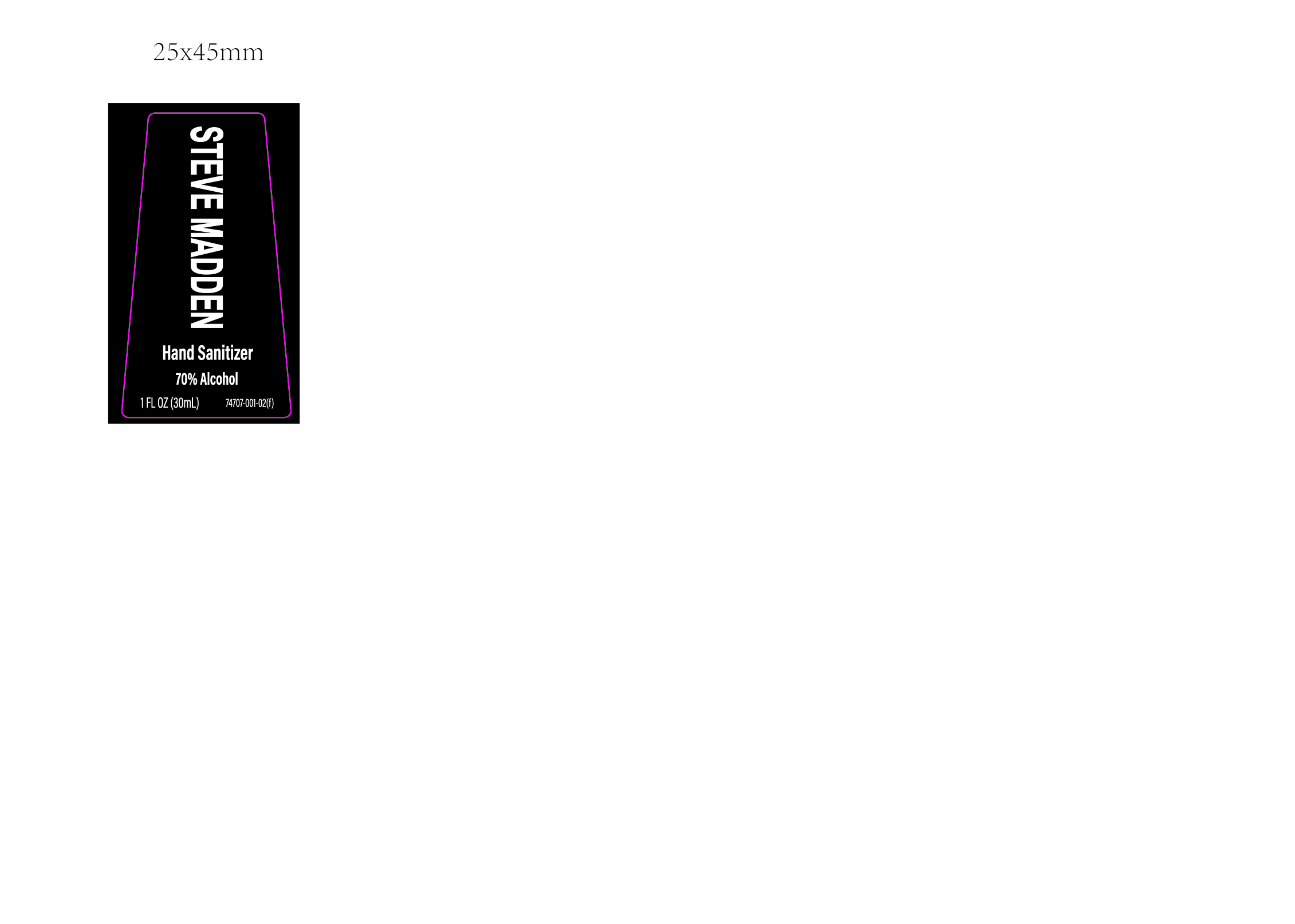 DRUG LABEL: Hand Sanitizer
NDC: 74707-001 | Form: LIQUID
Manufacturer: Virus Protection Systems LLC
Category: otc | Type: HUMAN OTC DRUG LABEL
Date: 20200525

ACTIVE INGREDIENTS: ALCOHOL 70 mL/100 mL
INACTIVE INGREDIENTS: GLYCERIN 0.4 mL/100 mL; HYDROGEN PEROXIDE 0.4 mL/100 mL; WATER 29.2 mL/100 mL

Steve Madden Label 70% Alchohol Hand Sanitizer, 30ML

This is a hand sanitizer manufactured according to the Temporary Policy for Preparation of Certain Alcohol-Based Hand Sanitizer Products During the Public Health Emergency (CoViD-19); Guidance for Industry.

The hand sanitizer is manufactured using only the following United States Pharmacopoeia (USP) grade ingredients in the preparation of the product (percentage in final product formulation) consistent with World Health Organization (WHO) recommendations:

1. Alcohol (70%, v/v) in an aqueous solution denatured according to Alcohol and Tobacco Tax and Trade Bureau regulations in 27 CFR part 20.
2. Glycerol (.4% v/v).
3. Hydrogen peroxide (0.4% v/v).
4. Sterile distilled water or boiled cold water.

The firm does not add other active or inactive ingredients. Different or additional ingredients may impact the quality and potency of the product.

Active Ingredient(s)

Alcohol 70% v/v. Purpose: Antiseptic

Purpose

Antiseptic, Hand Sanitizer

Use

For hand-washing to decrease bacteria on the skin if soap and water is not available

Warnings

Flammable. Keep away from heat or flame

Do not use

in or near the eyes

Stop use and ask a doctor if irritation or redness develop.
Keep out of reach of children. If swallowed, get medical help or contact a Poison Control Center right away.

Stop use and ask a doctor if irritation or redness.

Keep out of reach of children. If swallowed, get medical help or contact a Poison Control Center right away.

Directions

- Wet hands thoroughly with product and rub together and allow to dry without wiping

Other information

- Store below 105 fahrenheit
- May discolor some fabrics

Inactive ingredients

Water, glycerin, carbomer, triethanolamine, denatonium, benzoate

Package Label - Principal Display Panel

Steve Madden

Hand Sanitizer

70% Alchohol

30 ml NDC: 74707-001-03